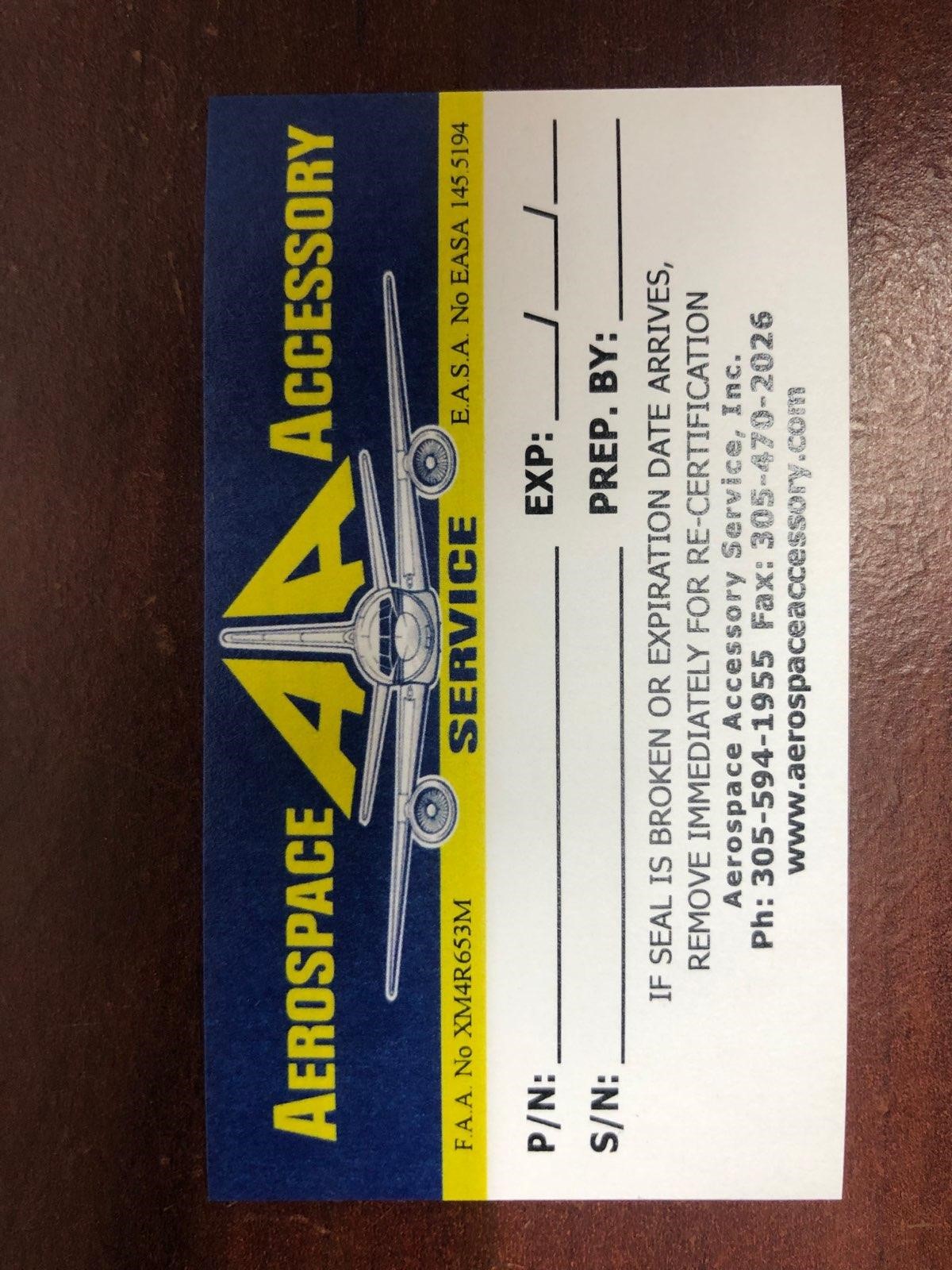 DRUG LABEL: Model MT2020-777 Model S6-01-0005-306 Model 011798 Model 011798-1494 Model 70004-00
NDC: 27860-008 | Form: KIT | Route: TOPICAL
Manufacturer: Aerospace Accessory Service, Inc
Category: other | Type: MEDICAL DEVICE
Date: 20210505

ACTIVE INGREDIENTS: POVIDONE-IODINE 10 mg/1 mL; AMMONIA 0.045 g/0.3 mL
INACTIVE INGREDIENTS: CITRIC ACID MONOHYDRATE; SODIUM PHOSPHATE, DIBASIC, ANHYDROUS; NONOXYNOL-9; SODIUM HYDROXIDE; WATER; ALCOHOL; FD&C RED NO. 40; WATER

Model MT2020-777
Model S6-01-0005-306
Model 011798
Model 011798-1494
Model 70004-00

Aerospace Accessory Service

P/N:

S/N:

EXP:

Prep. By: